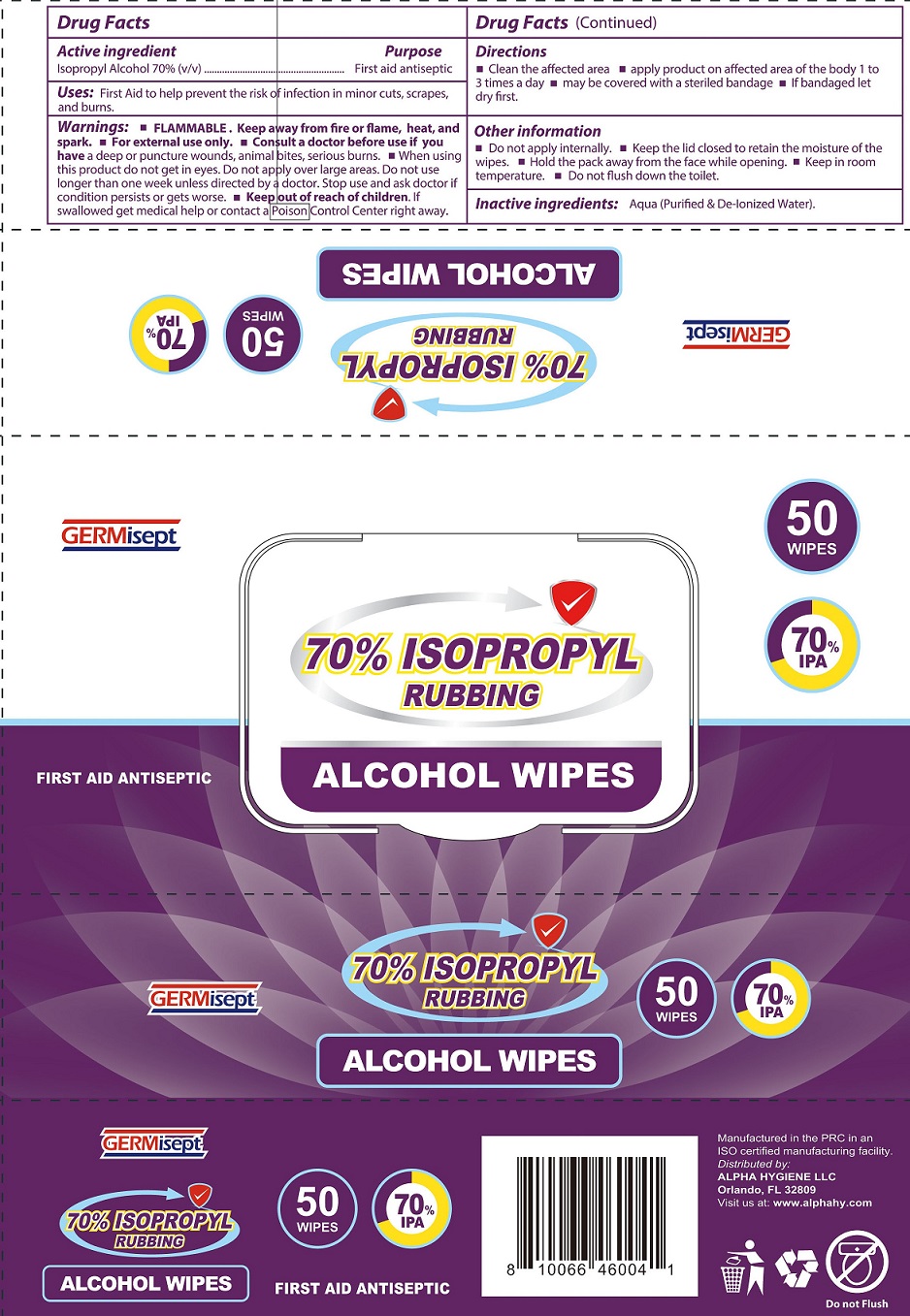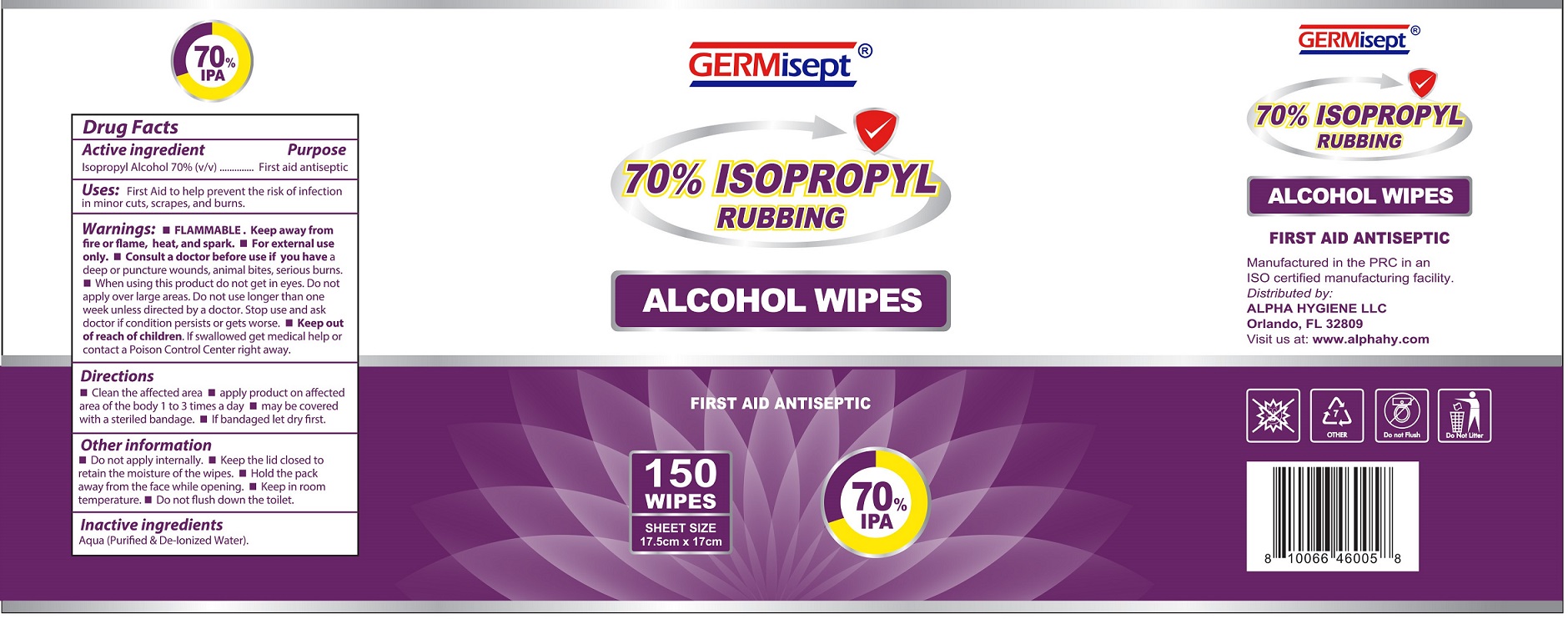 DRUG LABEL: GERMisept 70 Isopropyl Rubbing Alcohol Wipes
NDC: 80862-001 | Form: CLOTH
Manufacturer: Alpha Hygiene LLC
Category: otc | Type: HUMAN OTC DRUG LABEL
Date: 20210114

ACTIVE INGREDIENTS: ISOPROPYL ALCOHOL 70 mL/100 mL
INACTIVE INGREDIENTS: WATER

GERMisept 70% Isopropyl Rubbing Alcohol Wipes

Active ingredient

Isopropyl Alcohol 70% (v/v)

Pupose

First aid antiseptic

Uses:

First Aid to help prevent the risk of infection in minor cuts, scrapes, and burns

Warnings:

FLAMMABLE. Keep away from fire or flame, heat, and spark. For external use only. Consult a doctor before use if you have a deep or puncture wounds, animal bites, serious burns.

When using this product

do not get in eyes. Do not apply over large areas.

Do not use

longer than one week unless directed by a doctor.

Stop use and ask doctor

if condition persists or gets wrose.

Keep out of reach of children.

If swallowed get medical help or contact a Poison Control Center right away.

Directions

- Clean the affected area
- apply product on affected area of the body 1 to 3 times a day
- may be covered with a steriled bandage
- If bandaged let dry first.

Other information

- Do not apply internally.
- Keep the lid closed to retain the moisture of the wipes.
- Hold the pack away from the face while opening.
- Keep in room temperature.
- Do not flush down the toilet.

Inactive ingredients:

Aqua (Purified & De-Ionized Water).